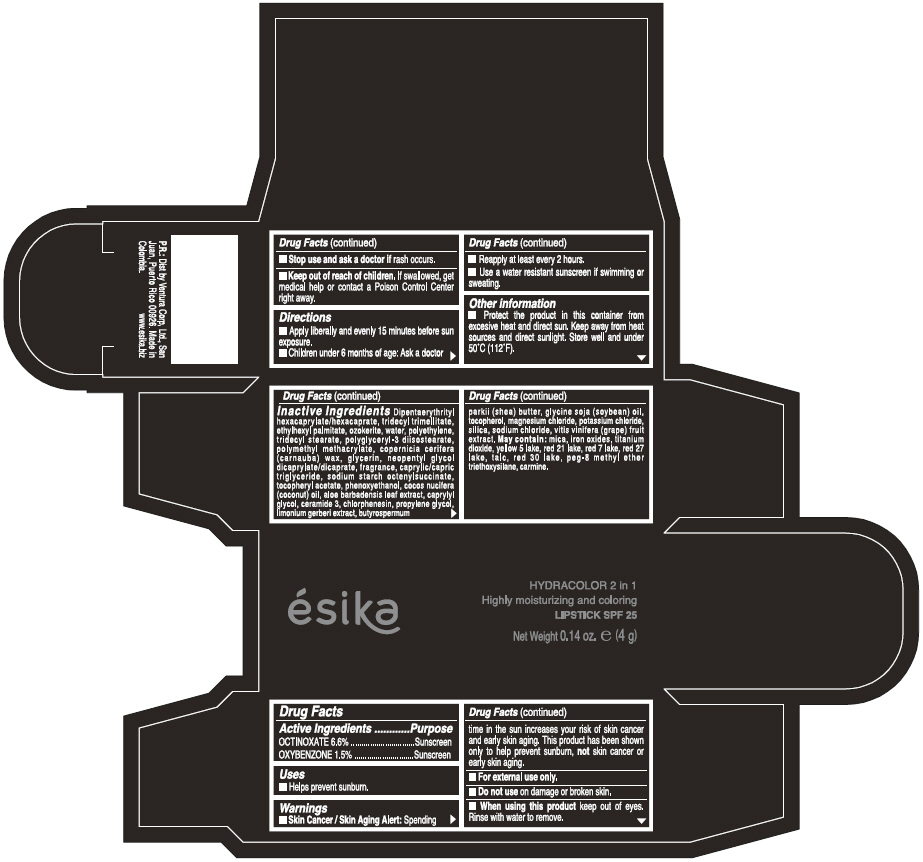 DRUG LABEL: ESIKA HYDRACOLOR 2 IN 1 Highly Moisturizing and coloring SPF 25
NDC: 13537-916 | Form: LIPSTICK
Manufacturer: Ventura Corporation LTD
Category: otc | Type: HUMAN OTC DRUG LABEL
Date: 20250409

ACTIVE INGREDIENTS: OCTINOXATE 0.066 g/1 g; OXYBENZONE 0.015 g/1 g
INACTIVE INGREDIENTS: DIPENTAERYTHRITYL HEXACAPRYLATE/HEXACAPRATE; TRIDECYL TRIMELLITATE; ETHYLHEXYL PALMITATE; WATER; HIGH DENSITY POLYETHYLENE; TRIDECYL STEARATE; POLYGLYCERYL-3 DIISOSTEARATE; CARNAUBA WAX; GLYCERIN; NEOPENTYL GLYCOL DICAPRYLATE/DICAPRATE; MEDIUM-CHAIN TRIGLYCERIDES; .ALPHA.-TOCOPHEROL ACETATE; PHENOXYETHANOL; COCONUT OIL; ALOE VERA LEAF; CAPRYLYL GLYCOL; CERAMIDE 3; CHLORPHENESIN; PROPYLENE GLYCOL; SHEA BUTTER; SOYBEAN OIL; TOCOPHEROL; MAGNESIUM CHLORIDE; POTASSIUM CHLORIDE; SILICON DIOXIDE; SODIUM CHLORIDE; WINE GRAPE; MICA; FERRIC OXIDE RED; TITANIUM DIOXIDE; FD&C YELLOW NO. 5; ALUMINUM OXIDE; D&C RED NO. 21; D&C RED NO. 7; D&C RED NO. 27; TALC; D&C RED NO. 30

ÉSIKA HYDRACOLOR 2 IN 1 Highly Moisturizing and coloring SPF 25

Drug Facts

ACTIVE INGREDIENT

Active Ingredients | Purpose
OCTINOXATE: 6.6% | Sunscreen
OXYBENZONE: 1.5% | Sunscreen

Uses

- Helps prevent sunburn.

Warnings

- Skin Cancer / Skin Aging Alert:Spending time in the sun increases your risk of skin cancer and early skin aging. This product has been shown only to help prevent sunburn, notskin cancer or early skin aging.
- For external use only.

- Do not useon damaged or broken skin.

WHEN USING

- When using this productkeep out of eyes.Rinse with water to remove.

- Stop use and ask a doctor ifrash occurs.

- Keep out of reach of children.If swallowed, get medical help or contact a Poison Control Center right away.

Directions

- Apply liberally and evenly 15 minutes before sun exposure.
- Reapply at least every 2 hours.
- Use a water resistant sunscreen if swimming or sweating.
- Children under 6 months of age: Ask a doctor

Other information

- Protect this product in this container form excesive heat and direct sun. Keep away from heat sources and direct sunlight. Store well and under 50°C (112°F).

Inactive ingredients

DIPENTAERYTHRITYL HEXACAPRYLATE/HEXACAPRATE, TRIDECYL TRIMELLITATE, ETHYLHEXYL PALMITATE, OZOKERITE, WATER, POLYETHYLENE, TRIDECYL STEARATE, POLYGLYCERYL-3 DIISOSTEARATE, POLYMETHYL METHACRYLATE, COPERNICIA CERIFERA (CARNAUBA) WAX, GLYCERIN, NEOPENTYL GLYCOL DICAPRYLATE/DICAPRATE, FRAGRANCE, CAPRYLIC/CAPRIC TRIGLYCERIDE, SODIUM STARCH OCTENYLSUCCINATE, TOCOPHERYL ACETATE, PHENOXYETHANOL, COCOS NUCIFERA (COCONUT) OIL, ALOE BARBADENSIS LEAF EXTRACT, CAPRYLYL GLYCOL, CERAMIDE 3, CHLORPHENESIN, PROPYLENE GLYCOL, LIMONIUM GERBERI EXTRACT, BUTYROSPERMUM PARKII (SHEA) BUTTER, GLYCINE SOJA OIL (GLYCINE SOJA (SOYBEAN) OIL), TOCOPHEROL, MAGNESIUM CHLORIDE, POTASSIUM CHLORIDE, SILICA, SODIUM CHLORIDE,VITIS VINIFERA (GRAPE) FRUIT EXTRACT

May contain:
MICA,IRON OXIDES, TITANIUM DIOXIDE, YELLOW 5 LAKE, RED 21 LAKE, RED 7 LAKE, RED 27 LAKE, TALC, RED 30 LAKE, PEG-8 METHYL ETHER TRIETHOXYSILANE, CARMINE.

P.R.:Dist. by Ventura Corp, Ltd., San
Juan, Puerto Rico 00926.

PRINCIPAL DISPLAY PANEL - 4 g Tube Box - (MARRON GLAMOUR) - BROWN

ésika

HYDRACOLOR 2 in 1
Highly moisturizing and coloring
LIPSTICK SPF 25

Net Weight 0.14 oz. e(4 g)

PRINCIPAL DISPLAY PANEL - 4 g Tube Box - (ROJO DESEO) - RED

ésika

HYDRACOLOR 2 in 1
Highly moisturizing and coloring
LIPSTICK SPF 25

Net Weight 0.14 oz. e(4 g)

PRINCIPAL DISPLAY PANEL - 4 g Tube Box - (ROJO INTRIGANTE) - RED

ésika

HYDRACOLOR 2 in 1
Highly moisturizing and coloring
LIPSTICK SPF 25

Net Weight 0.14 oz. e(4 g)

PRINCIPAL DISPLAY PANEL - 4 g Tube Box - (ROJO LUJURIA) - RED

ésika

HYDRACOLOR 2 in 1
Highly moisturizing and coloring
LIPSTICK SPF 25

Net Weight 0.14 oz. e(4 g)

PRINCIPAL DISPLAY PANEL - 4 g Tube Box - (CORAL CHIC) - PINK

ésika

HYDRACOLOR 2 in 1
Highly moisturizing and coloring
LIPSTICK SPF 25

Net Weight 0.14 oz. e(4 g)

PRINCIPAL DISPLAY PANEL - 4 g Tube Box - (ROSA ENCANTO) - PINK

ésika

HYDRACOLOR 2 in 1
Highly moisturizing and coloring
LIPSTICK SPF 25

Net Weight 0.14 oz. e(4 g)

PRINCIPAL DISPLAY PANEL - 4 g Tube Box - (BORGONA SEXY) - PURPLE

ésika

HYDRACOLOR 2 in 1
Highly moisturizing and coloring
LIPSTICK SPF 25

Net Weight 0.14 oz. e(4 g)

PRINCIPAL DISPLAY PANEL - 4 g Tube Box - (FUCSIA CAUTIVANTE) - PINK

ésika

HYDRACOLOR 2 in 1
Highly moisturizing and coloring
LIPSTICK SPF 25

Net Weight 0.14 oz. e(4 g)

PRINCIPAL DISPLAY PANEL - 4 g Tube Box - (GRANATE SEDUCTOR) - PURPLE

ésika

HYDRACOLOR 2 in 1
Highly moisturizing and coloring
LIPSTICK SPF 25

Net Weight 0.14 oz. e(4 g)

PRINCIPAL DISPLAY PANEL - 4 g Tube Box - (ROSA ROMANTICA) - PINK

ésika

HYDRACOLOR 2 in 1
Highly moisturizing and coloring
LIPSTICK SPF 25

Net Weight 0.14 oz. e(4 g)

PRINCIPAL DISPLAY PANEL - 4 g Tube Box - (NARANJA PRIMAVERA) - ORANGE

ésika

HYDRACOLOR 2 in 1
Highly moisturizing and coloring
LIPSTICK SPF 25

Net Weight 0.14 oz. e(4 g)

PRINCIPAL DISPLAY PANEL - 4 g Tube Box - (FRAMBUESA MANIA) - RED

ésika

HYDRACOLOR 2 in 1
Highly moisturizing and coloring
LIPSTICK SPF 25

Net Weight 0.14 oz. e(4 g)

PRINCIPAL DISPLAY PANEL - 4 g Tube Box - (ROSA DULZURA) - PINK

ésika

HYDRACOLOR 2 in 1
Highly moisturizing and coloring
LIPSTICK SPF 25

Net Weight 0.14 oz. e(4 g)

PRINCIPAL DISPLAY PANEL - 4 g Tube Box - (PIMIENTA CALIENTE) - BROWN

ésika

HYDRACOLOR 2 in 1
Highly moisturizing and coloring
LIPSTICK SPF 25

Net Weight 0.14 oz. e(4 g)

PRINCIPAL DISPLAY PANEL - 4 g Tube Box - (CANELA NUDE) - ORANGE

ésika

HYDRACOLOR 2 in 1
Highly moisturizing and coloring
LIPSTICK SPF 25

Net Weight 0.14 oz. e(4 g)

PRINCIPAL DISPLAY PANEL - 4 g Tube Box - (MORA GLAM) - BROWN

ésika

HYDRACOLOR 2 in 1
Highly moisturizing and coloring
LIPSTICK SPF 25

Net Weight 0.14 oz. e(4 g)

PRINCIPAL DISPLAY PANEL - 4 g Tube Box - (CORAL INTENSE) - RED

ésika

HYDRACOLOR 2 in 1
Highly moisturizing and coloring
LIPSTICK SPF 25

Net Weight 0.14 oz. e(4 g)

PRINCIPAL DISPLAY PANEL - 4 g Tube Box - (FRESA COQUETA) - RED

ésika

HYDRACOLOR 2 in 1
Highly moisturizing and coloring
LIPSTICK SPF 25

Net Weight 0.14 oz. e(4 g)

PRINCIPAL DISPLAY PANEL - 4 g Tube Box - (PIMIENTA CALIENTE FEMME) - RED

ésika

HYDRACOLOR 2 in 1
Highly moisturizing and coloring
LIPSTICK SPF 25

Net Weight 0.14 oz. e(4 g)

PRINCIPAL DISPLAY PANEL - 4 g Tube Box - (GRANATE SEDUCTOR FEMME) - PURPLE

ésika

HYDRACOLOR 2 in 1
Highly moisturizing and coloring
LIPSTICK SPF 25

Net Weight 0.14 oz. e(4 g)

PRINCIPAL DISPLAY PANEL - 4 g Tube Box - (FUCSIA CAUTIVANTE FEMME) - PINK

ésika

HYDRACOLOR 2 in 1
Highly moisturizing and coloring
LIPSTICK SPF 25

Net Weight 0.14 oz. e(4 g)

PRINCIPAL DISPLAY PANEL - 4 g Tube Box - (ROSA ROMANTICA FEMME) - PINK

ésika

HYDRACOLOR 2 in 1
Highly moisturizing and coloring
LIPSTICK SPF 25

Net Weight 0.14 oz. e(4 g)

PRINCIPAL DISPLAY PANEL - 4 g Tube Box - (ROJO INTRIGANTE FEMME) - RED

ésika

HYDRACOLOR 2 in 1
Highly moisturizing and coloring
LIPSTICK SPF 25

Net Weight 0.14 oz. e(4 g)

PRINCIPAL DISPLAY PANEL - 4 g Tube Box - (ROSA ENCANTO FEMME) - PINK

ésika

HYDRACOLOR 2 in 1
Highly moisturizing and coloring
LIPSTICK SPF 25

Net Weight 0.14 oz. e(4 g)